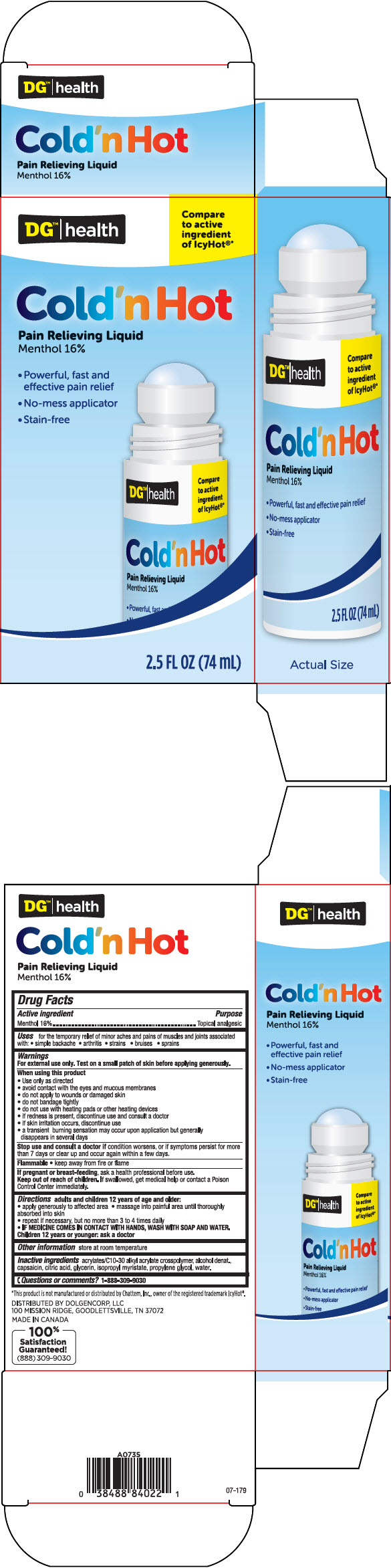 DRUG LABEL: DG Health Cold n Hot Pain Relieving
NDC: 55910-883 | Form: LIQUID
Manufacturer: Dolgencorp Inc
Category: otc | Type: HUMAN OTC DRUG LABEL
Date: 20241030

ACTIVE INGREDIENTS: Menthol, Unspecified Form 160 mg/1 mL
INACTIVE INGREDIENTS: Carbomer Interpolymer Type A (Allyl Sucrose Crosslinked); Alcohol; Capsaicin; Citric Acid Monohydrate; Glycerin; Isopropyl Myristate; Propylene Glycol; Water

DG™ Health Cold 'n Hot Pain Relieving Liquid
Topical Analgesic

Drug Facts

Active ingredients

Menthol 16%

Purpose

Topical analgesic

Uses

for the temporary relief of minor aches and pains of muscles and joints associated with:

- simple backache
- arthritis
- strains
- bruises
- sprains

Warnings

For external use only. Test on a small patch of skin before applying generously.

When using this product

- use only as directed
- avoid contact with the eyes and mucous membranes
- do not apply to wounds or damaged skin
- do not bandage tightly
- do not use with heating pads or other heating devices
- if redness is present, discontinue use and consult a doctor
- if skin irritation occurs, discontinue use
- a transient burning sensation may occur upon application but generally disappears in several days

Stop use and consult a doctor if condition worsens, or if symptoms persist for more than 7 days or clear up and occur again within a few days.

Flammable

- keep away from fire or flame

PREGNANCY OR BREAST FEEDING

If pregnant or breast-feeding, ask a health professional before use.

Keep out of reach of children. If swallowed, get medical help or contact a Poison Control Center immediately.

Directions

adults and children 12 years of age and older:

- apply generously to affected area
- massage into painful area until thoroughly absorbed into skin
- repeat if necessary, but not more than 3 to 4 times daily
- IF MEDICINE COMES IN CONTACT WITH HANDS, WASH WITH SOAP AND WATER.

Children 12 years or younger: ask a doctor

Other information

store at room temperature

Inactive ingredients

acrylates/C10-30 alkyl acrylate crosspolymer, alcohol denat., capsaicin, citric acid, glycerin, isopropyl myristate, propylene glycol, water.

Questions or comments?

1-888-309-9030

DISTRIBUTED BY DOLGENCORP, LLC
100 MISSION RIDGE, GOODLETTSVILLE, TN 37072

PRINCIPAL DISPLAY PANEL - 74 mL Bottle Carton

DG™ | health

Compare
to active
ingredient
of IcyHot®*

Cold'n Hot

Pain Relieving Liquid
Menthol 16%

- Powerful, fast and
  effective pain relief
- No-mess applicator
- Stain-free

2.5 FL OZ (74 mL)